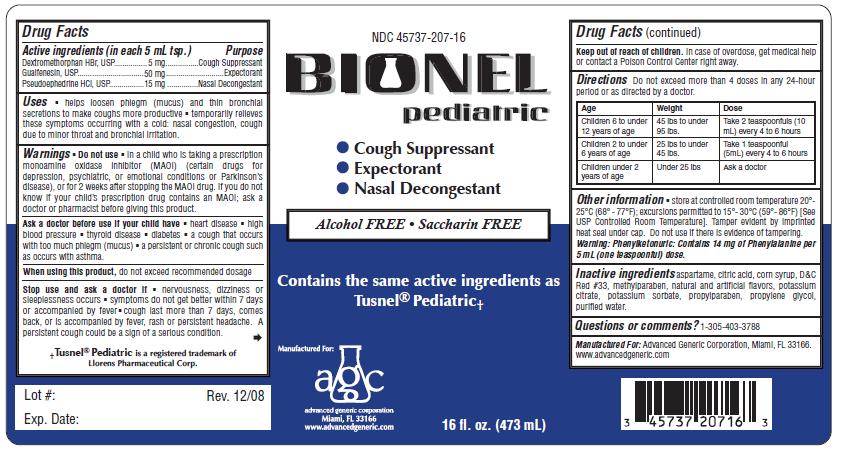 DRUG LABEL: Bionel
NDC: 45737-207 | Form: LIQUID
Manufacturer: Advanced Generic Corporation
Category: otc | Type: HUMAN OTC DRUG LABEL
Date: 20241220

ACTIVE INGREDIENTS: DEXTROMETHORPHAN HYDROBROMIDE 5 mg/5 mL; GUAIFENESIN 50 mg/5 mL; PSEUDOEPHEDRINE HYDROCHLORIDE 15 mg/5 mL
INACTIVE INGREDIENTS: CORN SYRUP; WATER; POTASSIUM CITRATE; POTASSIUM SORBATE; PROPYLENE GLYCOL; PROPYLPARABEN; CITRIC ACID MONOHYDRATE; ASPARTAME; METHYLPARABEN; D&C RED NO. 33

AGC-BionelPed 207

Active Ingredients: (in each 5 mL tsp.) Purpose

Guaifenesin 50 mg .............................................. Expectorant
Dextromethorphan Hydrobromide 5 mg.................. Cough Suppressant
Pseudoephedrine HCl 15 mg.................................. Nasal Decongestant

Uses

- helps loosen phlegm (mucus) and thin bronchial secretions to make coughs more productive
- temporarily relieves these symptoms occurring with a cold: nasal congestion, cough due to minor throat and bronchial irritation.

Warnings
Do not usein a child who is taking a prescription
Monoamine Oxidase Inhibitor (MAOI) (certain drugs for depression,
psychiatric, or emotional conditions or Parkinson’s disease), or for
2 weeks after stopping the MAOI drug. If you do not know if you are
taking a prescription drug that contains a MAOI; ask a doctor or
pharmacist before taking this product.

Ask a doctor before use if your child hav

e

- heart disease
- high blood pressure
- thyroid disease
- diabetes
- difficulty in urination due to the enlargement of the prostate gland
- a cough that occurs with too much phlegm (mucus)
- a breathing problem or chronic cough that lasts or occurs with smoking, asthma, chronic bronchitis, or emphysema. A persistent cough may be a sign of a serious condition.

Stop use and ask a doctor if

- you get nervous, dizzy or sleepless
- symptoms do not get better within 7 days or accompanied by fever
- cough lasts more than 7 days, comes back or is accompanied by fever, rash or persistent headache. These could be signs of a serious condition.

Keep out of reach of children.

PREGNANCY OR BREAST FEEDING

If pregnant or breast-feeding,ask a health professional before use.

DOSAGE AND ADMINISTRATION

Directions Do not exceed more than 4 doses in any 24-hour period or as directed by a doctor.

Children 6 to under 12 years of age; 45 lbs to under 95 lbs; Take 2 teaspoonfuls (10mL) every 4 to 6 hours

Children 2 to under 6 years of age; 25 lbs to under 45 lbs; Take 1 teaspoonful (5mL) every 4 to 6 hours

Children under 2 years of age; Under 25 lbs; Ask a doctor

Other information

- store at controlled room temperature 20°- 25°C (68° - 77°F); excursion permitted to 15°- 30°C (59°- 86°F) [See USP Controlled Room Temperature]. Tamper evident by imprinted heat seal under cap. Do not use if there is evidence of tampering.

Warning: Phenylketonuric: Contains 14 mg of Phenylalanine per 5 mL (one teaspoonful) dose.

INACTIVE INGREDIENT

Inactive ingredientsaspartame, citric acid, corn syrup, D and C Red No 33, methylparaben, natural and artificial flavors, potassium citrate, potassium sorbate, propylparaben, propylene glycol, purified water.

Questions or comments?1-305-403-3788

Manufactured For:Advanced Generic Corporation, Miami, Fl 33166

www.advancedgeneric.com